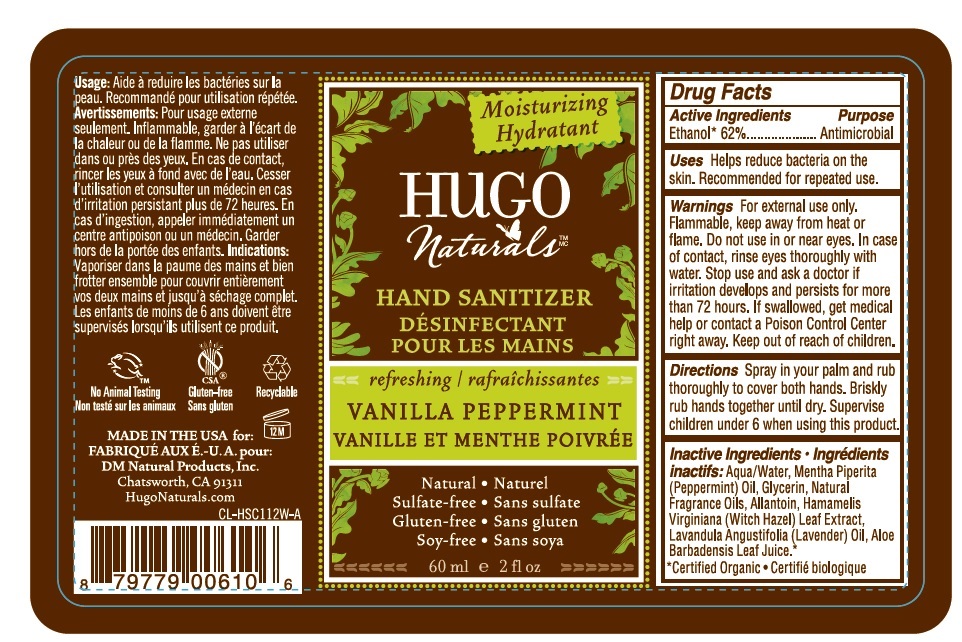 DRUG LABEL: HUGO Naturals
NDC: 70279-610 | Form: SPRAY
Manufacturer: Dm Natural Products, Inc.
Category: otc | Type: HUMAN OTC DRUG LABEL
Date: 20170705

ACTIVE INGREDIENTS: ALCOHOL 62 mL/100 mL
INACTIVE INGREDIENTS: WATER; PEPPERMINT OIL; GLYCERIN; ALLANTOIN; HAMAMELIS VIRGINIANA LEAF; LAVENDER OIL; ALOE VERA LEAF

HUGO Naturals VANILLA PEPPERMINT HAND SANITIZER

Active Ingredients

Ethanol* 62%

Purpose

Antimicrobial

INDICATIONS AND USAGE

Uses Helps reduce bacteria on the skin. Recommended for repeated use.

WARNINGS

Warnings For external use only. Flammable, keep away from heat or flame. Do not use in or near eyes. In case of contact, rinse eyes thoroughly with water. Stop use and ask a doctor if irritation develops and persists for more than 72 hours.

KEEP OUT OF REACH OF CHILDREN

If swallowed, get medical help or contact a Poison Control Center right away. Keep out of reach of children.

DOSAGE AND ADMINISTRATION

Directions Spray in your palm and rub thoroughly to cover both hands. Briskly rub hands together until dry. Supervise children under 6 when using this product.

INACTIVE INGREDIENT

Inactive Ingredients: Aqua/Water, Mentha Piperita (Peppermint) Oil, Glycerin, Natural Fragrance Oils, Allantoin, Hamamelis Virginiana (Witch Hazel) Leaf Extract, Lavandula Angustifolia (Lavender) Oil, Aloe Barbadensis Leaf Juice.*

*Certified Organic

Moisturizing

Natural

Sulfate-free

Gluten-free

Soy-free

No Animal Testing

Recyclable

MADE IN THE USA for:

DM Natural Products, Inc.

Chatsworth, CA 91311

HugoNaturals.com